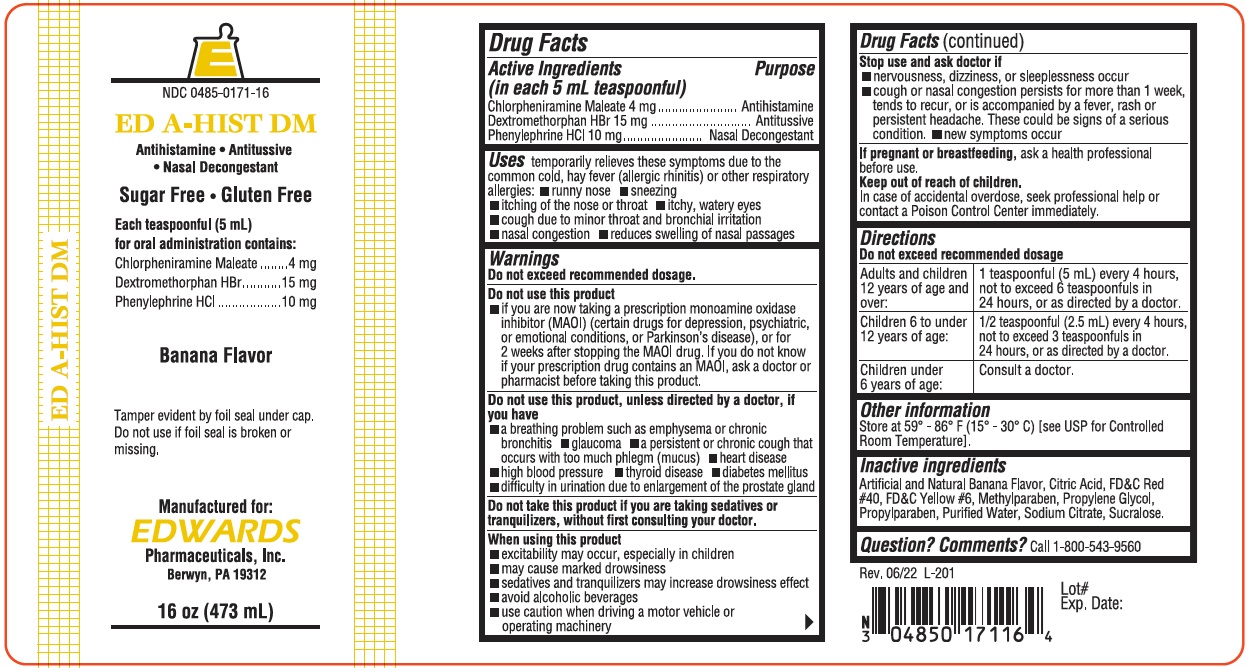 DRUG LABEL: ED A-HIST DM
NDC: 0485-0171 | Form: LIQUID
Manufacturer: EDWARDS PHARMACEUTICALS, INC.
Category: otc | Type: HUMAN OTC DRUG LABEL
Date: 20251231

ACTIVE INGREDIENTS: DEXTROMETHORPHAN HYDROBROMIDE 15 mg/5 mL; CHLORPHENIRAMINE MALEATE 4 mg/5 mL; PHENYLEPHRINE HYDROCHLORIDE 10 mg/5 mL
INACTIVE INGREDIENTS: FD&C RED NO. 40; FD&C YELLOW NO. 6; METHYLPARABEN; PROPYLPARABEN; PROPYLENE GLYCOL; WATER; SODIUM CITRATE; SUCRALOSE; CITRIC ACID MONOHYDRATE

ED-EDA-HISTDM 0171

Drug Facts

ACTIVE INGREDIENT

Active Ingredients (in each 5 mL teaspoonful) | Purpose
Chlorpheniramine Maleate 4 mg | Antihistamine
Dextromethorphan HBr 15 mg | Antitussive
Phenylephrine HCl 10 mg | Nasal Decongestant

Uses

temporarily relieves these symptoms due to the common cold, hay fever (allergic rhinitis) or other respiratory allergies:

- runny nose
- sneezing
- itching of the nose or throat
- itchy, watery eyes
- cough due to minor throat and bronchial irritation
- nasal congestion
- reduces swelling of nasal passages

Warnings

Do not exceed recommended dosage.

Do not use this product

- if you are now taking a prescription monoamine oxidase inhibitor (MAOI) (certain drugs for depression, psychiatric, or emotional conditions, or Parkinson's disease), or for 2 weeks after stopping the MAOI drug. If you do not know if your prescription drug contains an MAOI, ask a doctor or pharmacist before taking this product.

Do not use this product, unless directed by a doctor, if you have

- a breathing problem such as emphysema or chronic bronchitis
- glaucoma
- a persistent or chronic cough that occurs with too much phlegm (mucus)
- heart disease
- high blood pressure
- thyroid disease
- diabetes mellitus
- difficulty in urination due to enlargement of the prostate gland

Do not take this product if you are taking sedatives or tranquilizers, without first consulting your doctor.

When using this product

- excitability may occur, especially in children
- may cause marked drowsiness
- sedatives and tranquilizers may increase drowsiness effect
- avoid alcoholic beverages
- use caution when driving a motor vehicle or operating machinery

Stop use and ask doctor if

- nervousness, dizziness, or sleeplessness occur
- cough or nasal congestion persists for more than 1 week, tends to recur, or is accompanied by a fever, rash or persistent headache. These could be signs of a serious condition.
- new symptoms occur

PREGNANCY OR BREAST FEEDING

If pregnant or breastfeeding,ask a health professional before use.

Keep out of reach of children.

In case of accidental overdose, seek professional help or contact a Poison Control Center immediately.

Directions

Do not exceed recommended dosage

Adults and children 12 years of age and over: | 1 teaspoonful (5 mL) every 4 hours, not to exceed 6 teaspoonfuls in 24 hours, or as directed by a doctor.
Children 6 to under 12 years of age: | 1/2 teaspoonful (2.5 mL) every 4 hours, not to exceed 3 teaspoonfuls in 24 hours, or as directed by a doctor.
Children under 6 years of age: | Consult a doctor.

Other information

Store at 59° - 86° F (15° - 30° C) [see USP for Controlled Room Temperature].

Inactive ingredients

Artificial and Natural Banana Flavor, Citric Acid, FD&C Red #40, FD&C Yellow #6, Methyl Paraben, Propyl Paraben, Propylene Glycol, Purified Water, Sodium Citrate, Sucralose.

Question? Comments?

Call 1-800-543-9560

PRINCIPAL DISPLAY PANEL - 473 mL Bottle Label

E

NDC 0485-0171-16

ED A-HIST DM

Antihistamine • Antitussive
• Nasal Decongestant

Sugar Free • Gluten Free

Each teaspoonful (5 mL)
for oral administration contains:
Chlorpheniramine Maleate 4 mg
Dextromethorphan HBr 15 mg
Phenylephrine HCl 10 mg

Banana Flavor

Tamper evident by foil seal under cap.
Do not use if foil seal is broken or
missing.

Manufactured for:
EDWARDS
Pharmaceuticals, Inc.
Ripley, MS 38663

16oz. (473 mL)